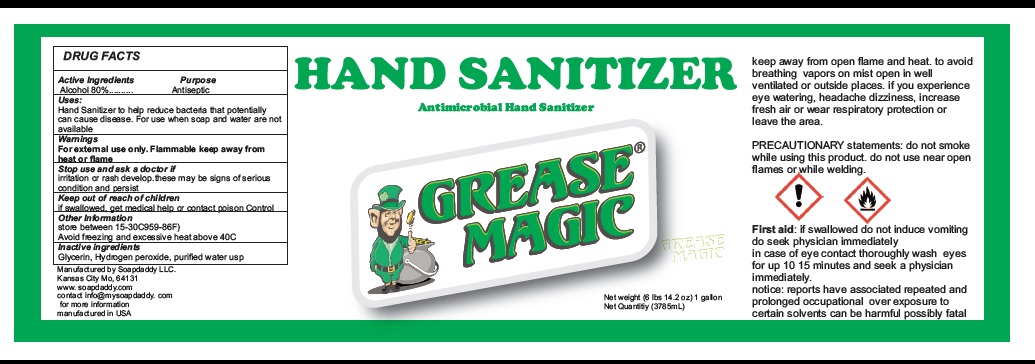 DRUG LABEL: GREASE MAGIC HAND SANIITIZER
NDC: 90064-001 | Form: GEL
Manufacturer: NU-TECH CLEANING SYSTEMS, INC.
Category: otc | Type: HUMAN OTC DRUG LABEL
Date: 20220126

ACTIVE INGREDIENTS: ALCOHOL 80 mL/100 mL
INACTIVE INGREDIENTS: GLYCERIN; HYDROGEN PEROXIDE; WATER

Active Ingredient

Alcohol 80% v/v.

Purpose

Antiseptic

Uses

Hand Sanitizer to help reduce bacteria that potentially can cause disease. For use when soap and water are not available.

Warnings

For external use only. Flammable keep away from heat or flame.

Do not use if irritation or rash develop. these may be signs of serious condition and persist.

when using this product do not smoke

Keep out of reach of children. If swallowed, get medical help or contact a Poison Control .

Inactive ingredients

Glycerin, Hydrogen peroxide, purified water USP

Other information

store between 15-30C(59-86F). Avoid freezing and excessive heat above 40C.

Keep away from open flame and heat. to avoid breathing vapors on mist open in well ventilated or outside places. if you experience
eye watering, headache dizziness, increase fresh air or wear respiratory protection or leave the area.

PRECAUTIONARY statements: do not smoke while using this product. do not use near open flames or while welding.

First aid: if swallowed do not induce vomiting do seek physician immediately in case of eye contact thoroughly wash eyes for up 10 15 minutes and seek a physician immediately.
notice: reports have associated repeated and prolonged occupational over exposure to certain solvents can be harmful possibly fatal.